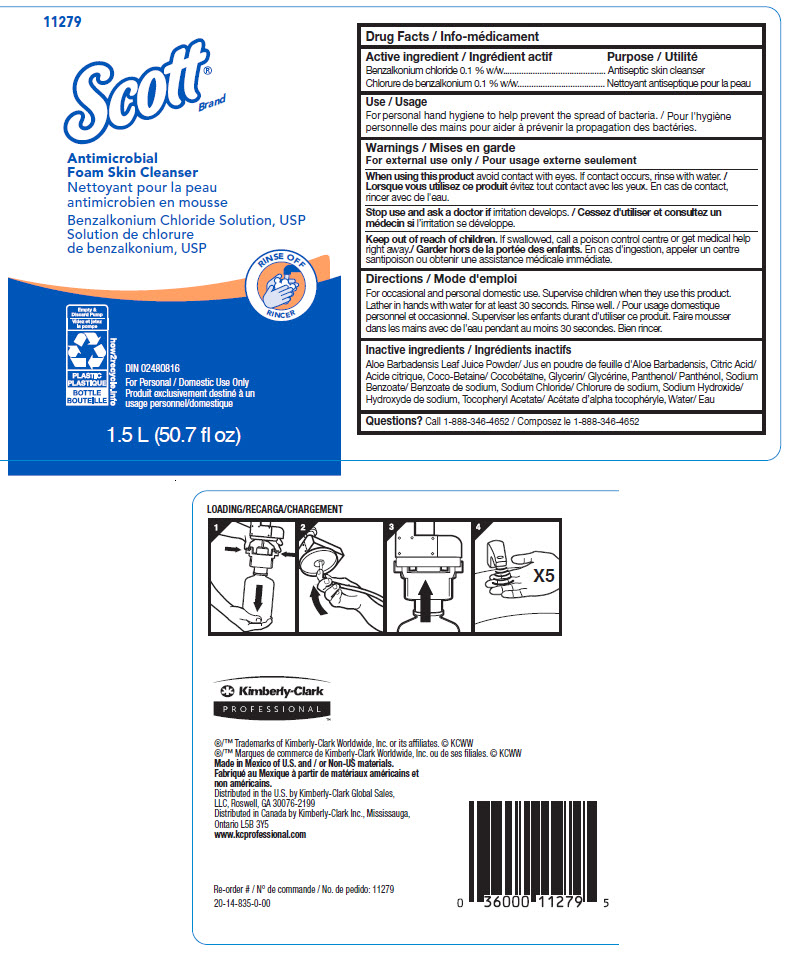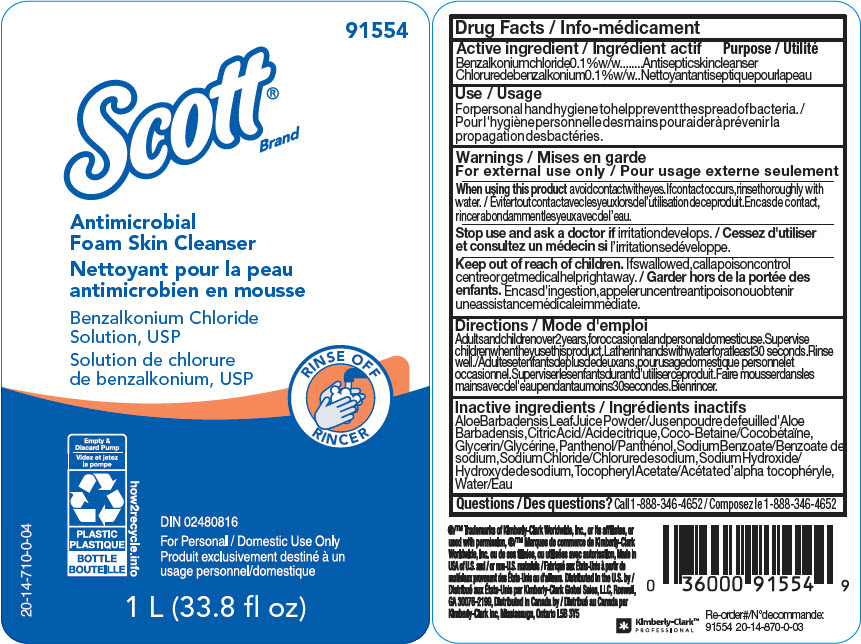 DRUG LABEL: SCOTT Antimicrobial Foam Skin Cleanser
NDC: 55118-800 | Form: SOLUTION
Manufacturer: Kimberly-Clark
Category: otc | Type: HUMAN OTC DRUG LABEL
Date: 20250904

ACTIVE INGREDIENTS: Benzalkonium Chloride 1 mg/1000 mL
INACTIVE INGREDIENTS: Aloe; Citric Acid Monohydrate; Coco-Betaine; Glycerin; Panthenol; Sodium Benzoate; Sodium Chloride; Sodium Hydroxide; .Alpha.-Tocopherol Acetate; Water

SCOTT® Antimicrobial Foam Skin Cleanser

Drug Facts

Active ingredient

Benzalkonium chloride 0.1 % w/w

Purpose

Antiseptic skin cleanser

Use

For personal hand hygiene to help prevent the spread of bacteria.

Warnings

For external use only

When using this product avoid contact with eyes. If contact occurs, rinse with water.

Stop use and ask a doctor if irritation develops.

Keep out of reach of children. If swallowed, call a poison control centre or get medical help right away.

Directions

For occasional and personal domestic use. Supervise children when they use this product. Lather in hands with water for at least 30 seconds. Rinse well.

Inactive ingredients

Aloe Barbadensis Leaf Juice Powder, Citric Acid, Coco-Betaine, Glycerin, Panthenol, Sodium Benzoate, Sodium Chloride, Sodium Hydroxide, Tocopheryl Acetate, Water

Questions?

Call 1-888-346-4652

Distributed in the U.S. by Kimberly-Clark Global Sales,
LLC, Roswell, GA 30076-2199
Distributed in Canada by Kimberly-Clark Inc., Mississauga,
Ontario L5B 3Y5

PRINCIPAL DISPLAY PANEL - 1.5 L Bottle Label

11279

Scott®
Brand

Antimicrobial
Foam Skin Cleanser

Benzalkonium Chloride Solution, USP

RINSE OFF

Empty &
Discard Pump

PLASTIC

BOTTLE

how2recycle.info

DIN 02480816

For Personal / Domestic Use Only

1.5 L (50.7 fl oz)

PRINCIPAL DISPLAY PANEL - 1 L Bottle Label

91554

Scott®
Brand

Antimicrobial
Foam Skin Cleanser

Benzalkonium Chloride
Solution, USP

RINSE OFF

Empty &
Discard Pump

PLASTIC

BOTTLE

how2recycle.info

DIN 02480816

For Personal / Domestic Use Only

20-14-710-0-04

1 L (33.8 fl oz)